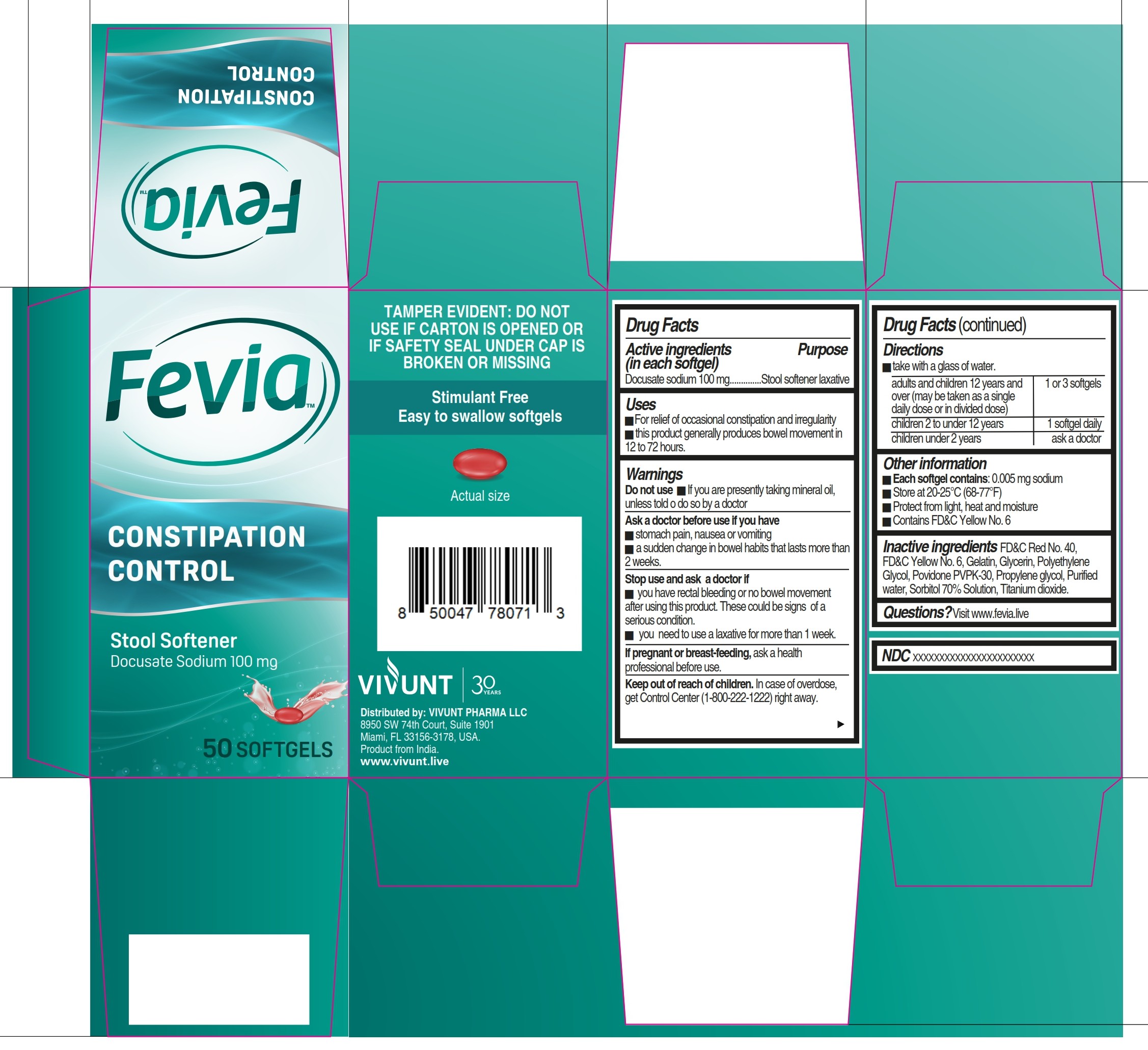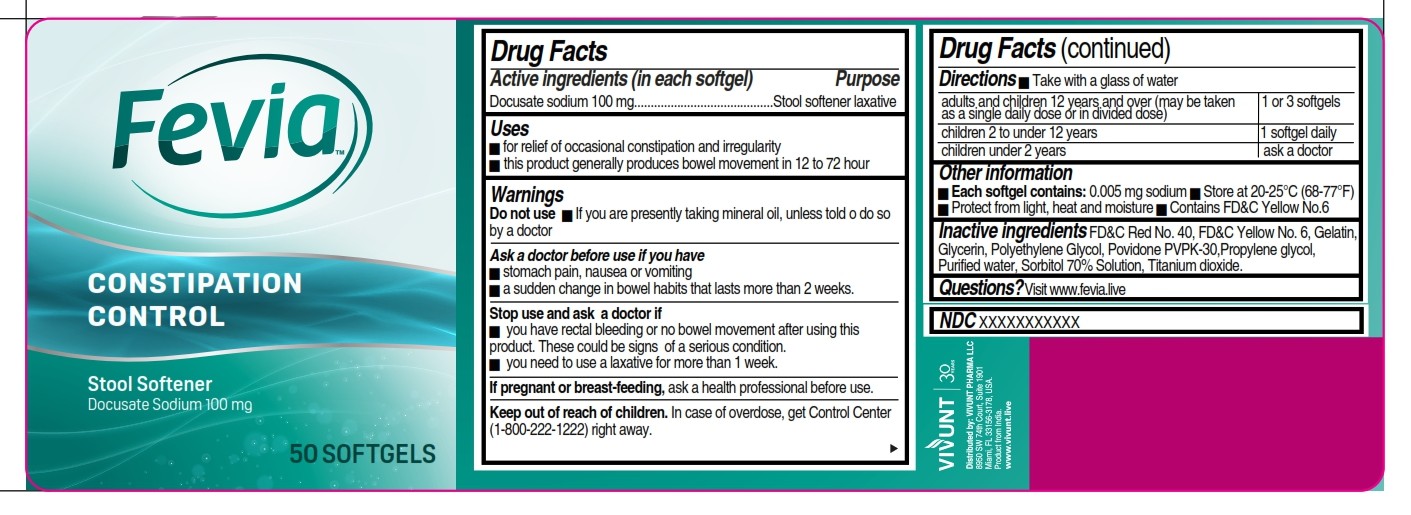 DRUG LABEL: FEVIA Constipation Control
NDC: 82706-029 | Form: CAPSULE, LIQUID FILLED
Manufacturer: VIVUNT PHARMA LLC
Category: otc | Type: HUMAN OTC DRUG LABEL
Date: 20260227

ACTIVE INGREDIENTS: DOCUSATE SODIUM 100 mg/1 1
INACTIVE INGREDIENTS: GLYCERIN; GELATIN; FD&C YELLOW NO. 6; FD&C RED NO. 40; POVIDONE K30; WATER; PROPYLENE GLYCOL; SORBITOL SOLUTION 70%; POLYETHYLENE GLYCOL, UNSPECIFIED; TITANIUM DIOXIDE

Fevia Constipation Control 50

Drug Facts

Active ingredients (in each softgel)

- Docusate sodium 100 mg

Purpose

- Stool softener laxative

Uses

- for relief of occasional constipation and irregularity
- this product generally produces bowel movement in 12 to 72 hour

Warnings

Do not use

- If you are presently taking mineral oil, unless told to do so by a doctor

Ask a doctor before use if you have

- stomach pain, nausea or vomiting
- a sudden change in bowel habits that lasts more than 2 weeks.

Stop use and ask a doctor if

- you have rectal bleeding or no bowel movement after using this product. These could be signs of a serious condition.
- you need to use a laxative for more than 1 week.

Stop use and ask a doctor if

- you have rectal bleeding or no bowel movement after using this prodct. These could be signs of a serious condition.
- you need to use a laxative for more than 1 week.

If pregnant or breast-feeding,

ask a health professional before use.

Keep out of reach of children

In case of overdose, get Control Center (1-800-222-1222) right away.

Directions

- Take with a glass of water

adults and children 12 years and over (may be taken as a single daily ose or in divided dose) | 1 or 3 softgels
children 2 to under 12 years | 1 softgel daily
children under 2 years | ask a doctor

Other information

- Each softgel contains: sodium 0.005 mg
- Store at 20-25°C (68-77°F)
- Protect from light, heat and moisture
- Contains FD&C Yellow No.6

Inactive ingredients

FD&C Red No. 40, FD&C Yellow No.6, Gelatin, Glycerin, Polyethylene Glycol, Povidone PVPK-30, Propylene glycol, Purified water, Sorbitol 70% Solution, Titanium dioxide.

Questions?

Visit www.fevia.live/contact

Distributed by

VIVUNT

Distributed by: VIVUNT PHARMA LLC

8950 SW 74th Court, Suite 1901

Miami, FL 33156-3178, USA.

Product from India

www.vivunt.live

Principal display panel

FEVIA™

CONSTIPATION CONTROL

Stool Softener

Docusate Sodium 100 mg

50 SOFTGELS

TAMPER EVIDENT: DO NOT USE IF CARTON IS OPENED OR IF SAFETY SEAL UNDER CAP IS BROKEN OR MISSING

Stimulant Free

Easy to swallow softgels

Actual size